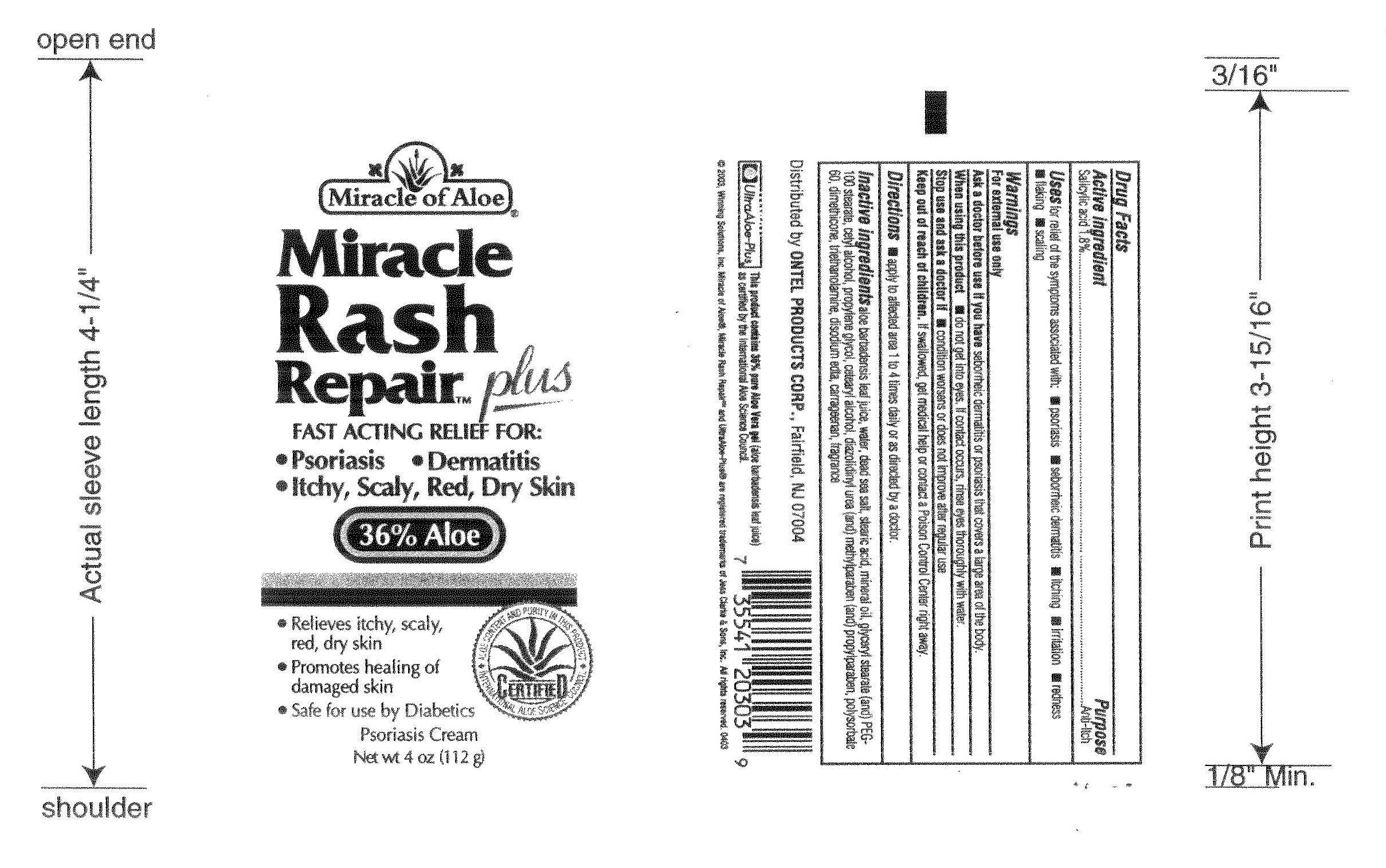 DRUG LABEL: Miracle Rash Repair  
NDC: 66391-0303 | Form: CREAM
Manufacturer: Winning Solutions
Category: otc | Type: HUMAN OTC DRUG LABEL
Date: 20110318

ACTIVE INGREDIENTS: SALICYLIC ACID 2.016 g/112 g
INACTIVE INGREDIENTS: Aloe vera Leaf  ; Water; Sea Salt; Stearic Acid; Mineral Oil; GLYCERYL MONOSTEARATE; PEG-100 STEARATE; Cetyl Alcohol; Propylene Glycol; CETOSTEARYL ALCOHOL; Diazolidinyl Urea; METHYLPARABEN; Propylparaben; Polysorbate 60; Dimethicone; TROLAMINE; EDETATE DISODIUM; Chondrus  

Active Ingredient : Salicylic Acid 1.8 %

Purpose : Anti - Itch

Warnings: For external use only .

Keep out of reach of children : If swallowed get medical help or contact a Poison Control Center right away.

INDICATIONS AND USAGE

Directions : apply to affected area 1 to 4 times daily or as directed by a doctor

INACTIVE INGREDIENT

aloe barabardensis leaf Juice , water , dead sea salt , stearic acid , mineral oil , glyceryl stearate , peg-100 sterate , cetyl alcohol , propylene glycol, cetearyl alcohol, diazolidinyl urea, methylparaben, propylparaben,polysorbate 60.dimethicone, triethanolamine, disodium edta , carageenan , fragrance

PACKAGE LABEL

Enter section text here